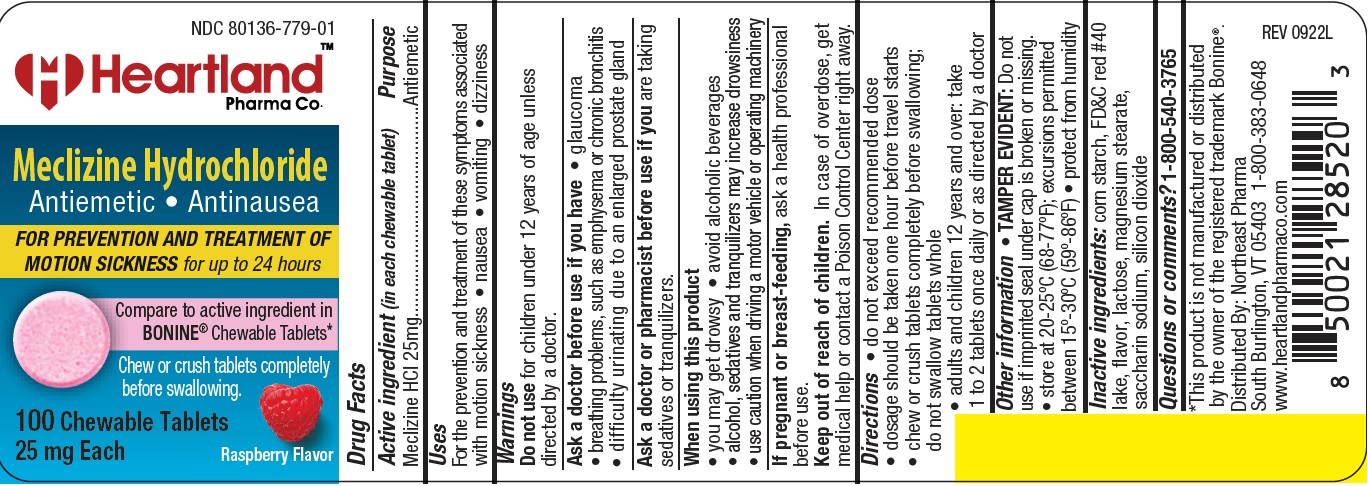 DRUG LABEL: Meclizine Hydrochloride
NDC: 80136-779 | Form: TABLET, CHEWABLE
Manufacturer: NORTHEAST PHARMA
Category: otc | Type: HUMAN OTC DRUG LABEL
Date: 20231026

ACTIVE INGREDIENTS: MECLIZINE HYDROCHLORIDE 25 mg/1 1
INACTIVE INGREDIENTS: STARCH, CORN; FD&C RED NO. 40; ANHYDROUS LACTOSE; MAGNESIUM STEARATE; SACCHARIN SODIUM; SILICON DIOXIDE

hpc 779

Active ingredient (in each chewable tablet)

Meclizine HCl 25 mg

Purpose

Antiemetic

Uses

For the prevention and treatment of these symptoms associated
with motion sickness • nausea • vomiting • dizziness

Warnings

Do not use

for children under 12 years of age unless directed by a doctor.

Ask a doctor before use if you have

- glaucoma
- breathing problems, such as emphysema or chronic bronchitis
- difficulty urinating due to an enlarged prostate gland

Ask a doctor or pharmacist before use if you are

taking sedatives or tranquilizers.

When using this product

- alcohol, sedatives, and tranquilizers may increase drowsiness
- drowsiness may occur
- avoid alcoholic beverages
- use caution when driving a motor vehicle or operating machinery

If pregnant or breast-feeding,

ask a health professional before use.

Keep out of reach of children.

In case of overdose, get medical help or contact a Poison Control Center right away.

Directions

- do not exceed recommended dose
- dosage should be taken one hour before travel starts
- chew or crush tablets completely before swallowing;do not swallow tablets whole
- adults and children 12 years and over: take 1 to 2 tablets once daily or as directed by a doctor

Other information

- TAMPER EVIDENT: Do not use if imprinted seal under cap is broken or missing.
- store at 20-25ºC (68-77ºF); excursions permitted between 15º-30ºC (59º-86ºF)
- protect from humidity

Inactive ingredients

corn starch, FD&C red #40 aluminum lake, flavor, lactose anhydrous, magnesium stearate, saccharin sodium, silicon dioxide

Questions or comments?

1-800-540-3765